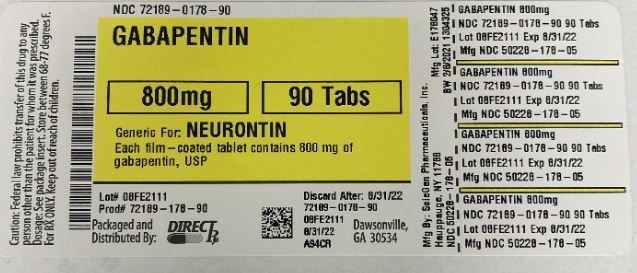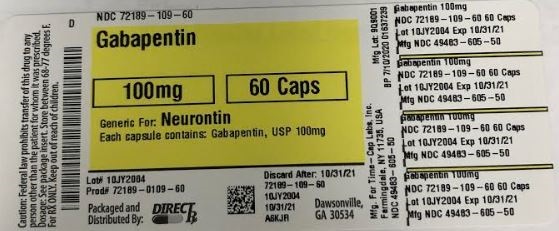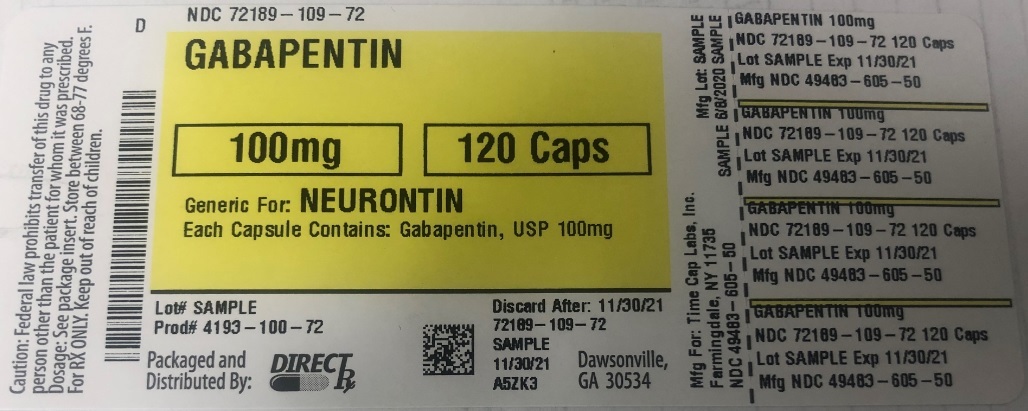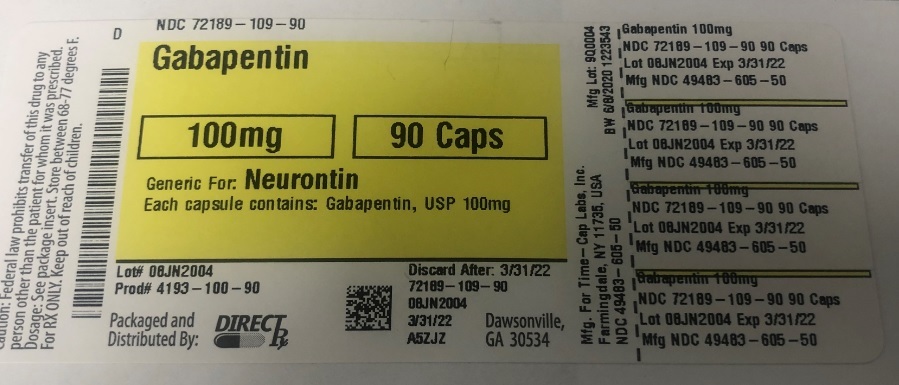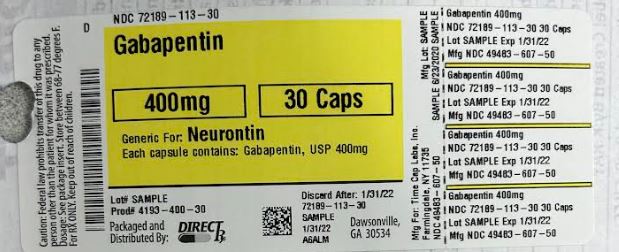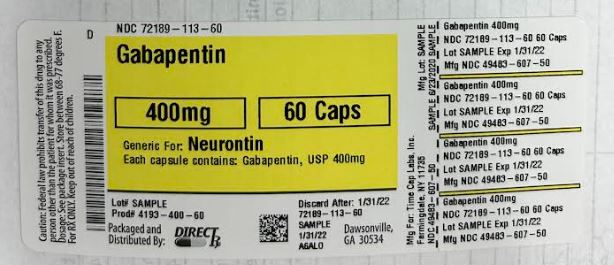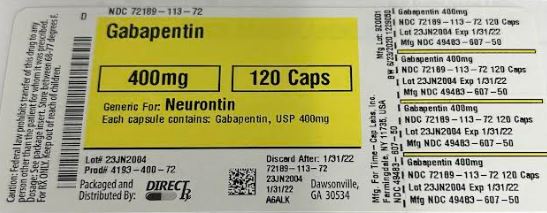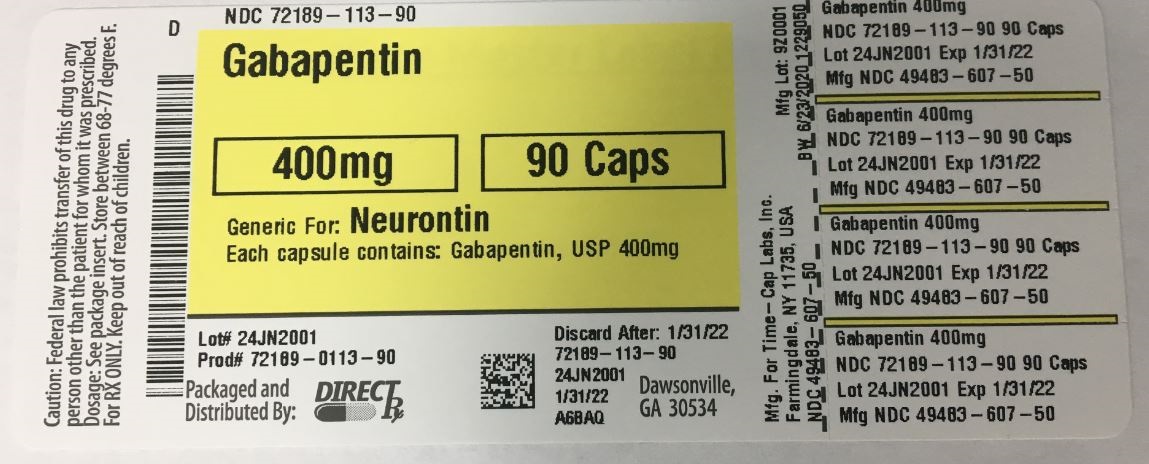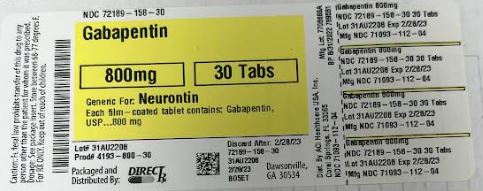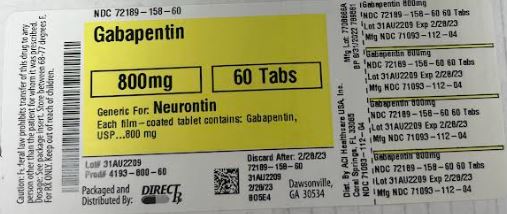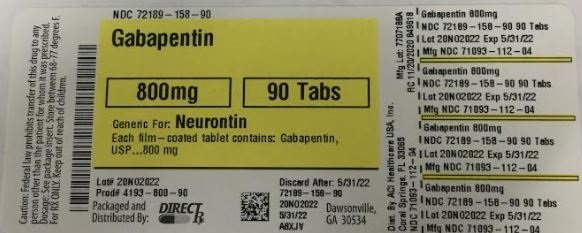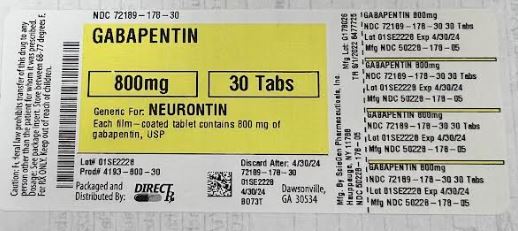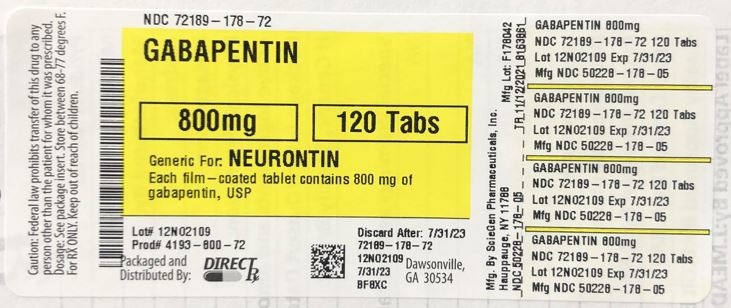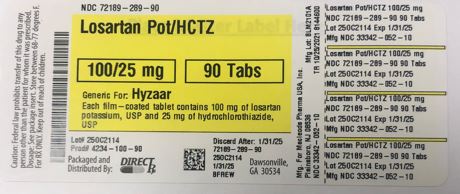 DRUG LABEL: GABAPENTIN
NDC: 72189-109 | Form: CAPSULE
Manufacturer: DIRECT RX
Category: prescription | Type: HUMAN PRESCRIPTION DRUG LABEL
Date: 20250117

ACTIVE INGREDIENTS: GABAPENTIN 100 mg/1 1
INACTIVE INGREDIENTS: TALC; LACTOSE MONOHYDRATE; STARCH, CORN; TITANIUM DIOXIDE; GELATIN; PROPYLENE GLYCOL; SHELLAC; FD&C BLUE NO. 2

GABAPENTIN

MEDICATION GUIDE

Gabapentin (gab'' a pen' tin)Capsules

What is the most important information I should know about gabapentin capsules?

Do not stop taking gabapentin capsules without first talking to your healthcare provider.

Stopping gabapentin capsules suddenly can cause serious problems.

Gabapentin capsules can cause serious side effects including:

1. Suicidal Thoughts. Like other antiepileptic drugs, gabapentin capsules may cause suicidal thoughts or actions in a very small number of people, about 1 in 500.

Call a healthcare provider right away if you have any of these symptoms, especially if they are new, worse, or worry you:

· thoughts about suicide or dying

· attempts to commit suicide

· new or worse depression

· new or worse anxiety

· feeling agitated or restless

· panic attacks

· trouble sleeping (insomnia)

· new or worse irritability

· acting aggressive, being angry, or violent

· acting on dangerous impulses

· an extreme increase in activity and talking (mania)

· other unusual changes in behavior or mood

How can I watch for early symptoms of suicidal thoughts and actions?

· Pay attention to any changes, especially sudden changes, in mood, behaviors, thoughts, or feelings.

· Keep all follow-up visits with your healthcare provider as scheduled.

Call your healthcare provider between visits as needed, especially if you are worried about symptoms.

Do not stop taking gabapentin capsules without first talking to a healthcare provider.

· Stopping gabapentin capsules suddenly can cause serious problems. Stopping a seizure medicine suddenly in a patient who has epilepsy can cause seizures that will not stop (status epilepticus).

· Suicidal thoughts or actions can be caused by things other than medicines. If you have suicidal thoughts or actions, your healthcare provider may check for other causes.

2. Changes in behavior and thinking -Using gabapentin capsules in children 3 to 12 years of age can cause emotional changes, aggressive behavior, problems with concentration, restlessness, changes in school performance, and hyperactivity.

3. Gabapentin capsules may cause a serious or life-threatening allergic reaction that may affect your skin or other parts of your body such as your liver or blood cells. This may cause you to be hospitalized or to stop gabapentin capsule. You may or may not have a rash with an allergic reaction caused by gabapentin capsule. Call a healthcare provider right away if you have any of

The following symptoms:

· skin rash

· hives

· difficulty breathing

· fever

· swollen glands that do not go away

· swelling of your face, lips, throat or tongue

· yellowing of your skin or of the whites of the eyes

· unusual bruising or bleeding

· severe fatigue or weakness

· unexpected muscle pain

· frequent infections

These symptoms may be the first signs of a serious reaction. A healthcare provider should examine you to decide if you should continue taking gabapentin capsules.

What are gabapentin capsules?

Gabapentin capsules are a prescription medicine used to treat:

· Pain from damaged nerves (postherpetic pain) that follows healing of shingles (a painful rash that comes after a herpes zoster infection) in adults.

· Partial seizures when taken together with other medicines in adults and children 3 years of age and older with seizures.

Who should not take gabapentin capsules?

Do not take gabapentin capsules if you are allergic to gabapentin or any of the other ingredients in gabapentin capsules. See the end of this Medication Guide for a complete list of ingredients in gabapentin capsules.

What should I tell my healthcare provider before taking gabapentin capsules?

Before taking gabapentin capsules, tell your healthcare provider if you:

· have or have had kidney problems or are on hemodialysis

· have or have had depression, mood problems, or suicidal thoughts or behavior

· have diabetes

· are pregnant or plan to become pregnant. It is not known if gabapentin capsules can harm your unborn baby. Tell your healthcare provider right away if you become pregnant while taking gabapentin capsules. You and your healthcare provider will decide if you should take gabapentin capsules while you are pregnant.

o Pregnancy Registry: If you become pregnant while taking gabapentin capsules, talk to your healthcare provider about registering with the North American Antiepileptic Drug (NAAED) Pregnancy Registry. The purpose of this registry is to collect information about the safety of antiepileptic drugs during pregnancy. You can enroll in this registry by calling 1-888-233-2334.

· are breast-feeding or plan to breast-feed. Gabapentin capsules can pass into breast milk. You and your healthcare provider should decide how you will feed your baby while you take gabapentin capsules.

Tell your healthcare provider about all the medicines you take, including prescription and over-the-counter medicines, vitamins, and herbal supplements.

Taking gabapentin capsules with certain other medicines can cause side effects or affect how well they work. Do not start or stop other medicines without talking to your healthcare provider.

Know the medicines you take. Keep a list of them and show it to your healthcare provider and pharmacist when you get a new medicine.

How should I take gabapentin capsules?

· Take gabapentin capsules exactly as prescribed. Your healthcare provider will tell you how much gabapentin capsules to take.

o Do not change your dose of gabapentin capsules without talking to your healthcare provider.

o Take gabapentin capsules with water.

· Gabapentin capsules can be taken with or without food. If you take an antacid containing aluminum and magnesium, such as Maalox®, Mylanta®, Gelusil®, Gaviscon® , or Di-Gel®, you should wait at least 2 hours before taking your next dose of gabapentin capsules.

If you take too much gabapentin capsules, call your healthcare provider or your local Poison Control Center right away at 1-800-222-1222.

What should I avoid while taking gabapentin capsules?

· Do not drink alcohol or take other medicines that make you sleepy or dizzy while taking gabapentin capsules without first talking with your healthcare provider. Taking gabapentin capsules with alcohol or drugs that cause sleepiness or dizziness may make your sleepiness or dizziness worse.

· Do not drive, operate heavy machinery, or do other dangerous activities until you know how gabapentin capsules affects you. Gabapentin capsules can slow your thinking and motor skills.

What are the possible side effects of gabapentin capsules?

Gabapentin capsules may cause serious side effects including:

See “What is the most important information I should know about gabapentin capsules?”

· problems driving while using gabapentin capsules. See “What I should avoid while taking gabapentin capsules?”

· sleepiness and dizziness which could increase the occurrence of accidental injury, including falls

· The most common side effects of gabapentin capsules include:

· lack of coordination • feeling tired

· viral infection • fever

· feeling drowsy • jerky movements

· nausea and vomiting • difficulty with coordination

· difficulty with speaking • double vision

· tremor • unusual eye movement

· swelling, usually of legs and feet

Tell your healthcare provider if you have any side effect that bothers you or that does not go away.

These are not all the possible side effects of gabapentin capsules. For more information, ask your healthcare provider or pharmacist.

Call your doctor for medical advice about side effects. You may report side effects to Time Cap Laboratories 1 877 290-4008 and/or FDA at 1-800-FDA-1088.

How should I store gabapentin capsules?

· Store gabapentin capsules between 68°F to 77°F (20°C to 25°C).

Keep gabapentin capsules and all medicines out of the reach of children.

General information about the safe and effective use of gabapentin capsules

Medicines are sometimes prescribed for purposes other than those listed in a Medication Guide. Do not use gabapentin capsules for a condition for which it was not prescribed. Do not give gabapentin capsules to other people, even if they have the same symptoms that you have. It may harm them.

This Medication Guide summarizes the most important information about gabapentin capsules. If you would like more information, talk with your healthcare provider. You can ask your healthcare provider or pharmacist for information about gabapentin capsules that was written for healthcare professionals.

What are the ingredients in gabapentin capsules?

Active ingredient: gabapentin, USP

Inactive ingredients in the capsules: lactose monohydrate, corn starch, and talc.

The 100 mg capsule shell contains gelatin and titanium dioxide.

The 300 mg capsule shell contains gelatin, titanium dioxide, and yellow iron oxide.

The 400 mg capsule shell contains gelatin, red iron oxide, titanium dioxide, and yellow iron oxide. The imprinting ink contains FD&C Blue No. 2, propylene glycol and shellac.

This Medication Guide has been approved by the U.S. Food and Drug Administration.

Rx only

Manufactured for:

Time-Cap-Labs, INC,

7 Michael Avenue, Farmingdale, NY 11735, USA

Manufactured by:

Marksans Pharma Ltd.

Plot No. L-82, L-83, Verna Indl. Estate,

Verna, Goa-403 722, India

Rev. 11/17

HOW SUPPLIED

100 mg Capsules (White/White colored, size '3' hard gelatin capsules with "103" printed on body of capsules containing white to off white granular powder) Bottles of 100 & 500